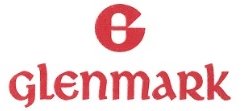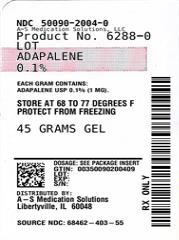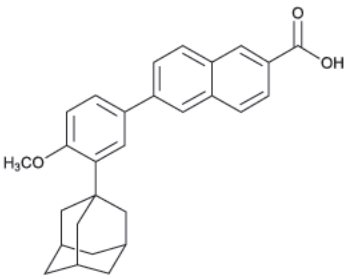 DRUG LABEL: Adapalene
NDC: 50090-2004 | Form: GEL
Manufacturer: A-S Medication Solutions
Category: prescription | Type: HUMAN PRESCRIPTION DRUG LABEL
Date: 20210825

ACTIVE INGREDIENTS: ADAPALENE 1 mg/1 g
INACTIVE INGREDIENTS: CARBOMER HOMOPOLYMER TYPE C (ALLYL PENTAERYTHRITOL CROSSLINKED); EDETATE DISODIUM; METHYLPARABEN; POLOXAMER 182; PROPYLENE GLYCOL; WATER; SODIUM HYDROXIDE

Adapalene Gel, 0.1%

Rx Only

DESCRIPTION

Adapalene gel 0.1%, containing adapalene USP, is used for the topical treatment of acne vulgaris. Each gram of adapalene gel 0.1% contains adapalene USP 0.1% (1 mg) in a vehicle consisting of carbomer homopolymer, edetate disodium, methylparaben, poloxamer 182, propylene glycol, purified water and sodium hydroxide.

The chemical name of adapalene USP is 6-[3-(1-adamantyl)-4-methoxyphenyl]-2-naphthoic acid. Adapalene USP is a white to off-white powder which is sparingly soluble in tetrahydrofuran, very slightly soluble in diethyl ether. The molecular formula is C28H28O3 and molecular weight is 412.52. Adapalene USP is represented by the following structural formula:

CLINICAL PHARMACOLOGY

Adapalene is a chemically stable, retinoid-like compound. Biochemical and pharmacological profile studies have demonstrated that adapalene is a modulator of cellular differentiation, keratinization, and inflammatory processes all of which represent important features in the pathology of acne vulgaris.

Mechanistically, adapalene binds to specific retinoic acid nuclear receptors but does not bind to the cytosolic receptor protein. Although the exact mode of action of adapalene is unknown, it is suggested that topical adapalene may normalize the differentiation of follicular epithelial cells resulting in decreased microcomedone formation.

Pharmacokinetics:

Absorption of adapalene through human skin is low. Only trace amounts (<0.25 ng/mL) of parent substance have been found in the plasma of acne patients following chronic topical application of adapalene in controlled clinical trials. Excretion appears to be primarily by the biliary route.

INDICATIONS AND USAGE

Adapalene gel, 0.1% is indicated for the topical treatment of acne vulgaris.

CONTRAINDICATIONS

Adapalene should not be administered to individuals who are hypersensitive to adapalene or any of the components in the vehicle gel.

WARNINGS

Use of adapalene gel should be discontinued if hypersensitivity to any of the ingredients is noted. Patients with sunburn should be advised not to use the product until fully recovered.

PRECAUTIONS

General

If a reaction suggesting sensitivity or chemical irritation occurs, use of the medication should be discontinued. Exposure to sunlight, including sunlamps, should be minimized during the use of adapalene. Patients who normally experience high levels of sun exposure, and those with inherent sensitivity to sun, should be warned to exercise caution. Use of sunscreen products and protective clothing over treated areas is recommended when exposure cannot be avoided. Weather extremes, such as wind or cold, also may be irritating to patients under treatment with adapalene. Avoid contact with the eyes, lips, angles of the nose, and mucous membranes. The product should not be applied to cuts, abrasions, eczematous skin, or sunburned skin.

Certain cutaneous signs and symptoms such as erythema, dryness, scaling, burning, or pruritus may be experienced during treatment. These are most likely to occur during the first two to four weeks and will usually lessen with continued use of the medication. Depending upon the severity of adverse events, patients should be instructed to reduce the frequency of application or discontinue use.

Drug Interactions

As adapalene gel has the potential to produce local irritation in some patients, concomitant use of other potentially irritating topical products (medicated or abrasive soaps and cleansers, soaps and cosmetics that have a strong drying effect, and products with high concentrations of alcohol, astringents, spices, or lime) should be approached with caution. Particular caution should be exercised in using preparations containing sulfur, resorcinol, or salicylic acid in combination with adapalene gel. If these preparations have been used, it is advisable not to start therapy with adapalene gel until the effects of such preparations in the skin have subsided.

Carcinogenesis, Mutagenesis, Impairment of Fertility

Carcinogenicity studies with adapalene have been conducted in mice at topical doses of 0.3, 0.9, and 2.6 mg/kg/day and in rats at oral doses of 0.15, 0.5, and 1.5 mg/kg/day, approximately 4-75 times the maximal daily human topical dose. In the oral study, positive linear trends were observed in the incidence of follicular cell adenomas and carcinomas in the thyroid glands of female rats, and in the incidence of benign and malignant pheochromocytomas in the adrenal medullas of male rats.

No photocarcinogenicity studies were conducted. Animal studies have shown an increased tumorigenic risk with the use of pharmacologically similar drugs (e.g., retinoids) when exposed to UV irradiation in the laboratory or to sunlight. Although the significance of these studies to human use is not clear, patients should be advised to avoid or minimize exposure to either sunlight or artificial UV irradiation sources.

In a series of in vivo and in vitro studies, adapalene did not exhibit mutagenic or genotoxic activities.

Pregnancy

Teratogenic effects

Pregnancy Category C. No teratogenic effects were seen in rats at oral doses of adapalene 0.15 to 5.0 mg/kg/day, up to 120 times the maximal daily human topical dose. Cutaneous route teratology studies conducted in rats and rabbits at doses of 0.6, 2.0, and 6.0 mg/kg/day, up to 150 times the maximal daily human topical dose exhibited no fetotoxicity and only minimal increases in supernumerary ribs in rats. There are no adequate and well-controlled studies in pregnant women. Adapalene should be used during pregnancy only if the potential benefit justifies the potential risk to the fetus.

Nursing Mothers

It is not known whether this drug is excreted in human milk. Because many drugs are excreted in human milk, caution should be exercised when adapalene gel is administered to a nursing woman.

Pediatric Use

Safety and effectiveness in pediatric patients below the age of 12 have not been established.

ADVERSE REACTIONS

Some adverse effects such as erythema, scaling, dryness, pruritus, and burning will occur in 10-40% of patients. Pruritus or burning immediately after application also occurs in approximately 20% of patients. The following additional adverse experiences were reported in approximately 1% or less of patients: skin irritation, burning/stinging, erythema, sunburn, and acne flares. These are most commonly seen during the first month of therapy and decrease in frequency and severity thereafter. All adverse effects with use of adapalene gel during clinical trials were reversible upon discontinuation of therapy.

OVERDOSAGE

Adapalene gel is intended for cutaneous use only. If the medication is applied excessively, no more rapid or better results will be obtained and marked redness, peeling, or discomfort may occur. The acute oral toxicity of adapalene gel in mice and rats is greater than 10 mL/kg. Chronic ingestion of the drug may lead to the same side effects as those associated with excessive oral intake of Vitamin A.

DOSAGE AND ADMINISTRATION

Adapalene gel 0.1% should be applied once a day to affected areas after washing in the evening before retiring. A thin film of the gel should be applied, avoiding eyes, lips, and mucous membranes.

During the early weeks of therapy, an apparent exacerbation of acne may occur. This is due to the action of the medication on previously unseen lesions and should not be considered a reason to discontinue therapy. Therapeutic results should be noticed after eight to twelve weeks of treatment.

HOW SUPPLIED

Product: 50090-2004

NDC: 50090-2004-0 45 g in a TUBE

Manufactured by:

Glenmark Pharmaceuticals Ltd.
Colvale-Bardez, Goa 403 513, India

Manufactured for:

Glenmark Pharmaceuticals Inc., USA
Mahwah, NJ 07430

Questions? 1 (888)721-7115
www.glenmarkpharma.com/usa

September 2014